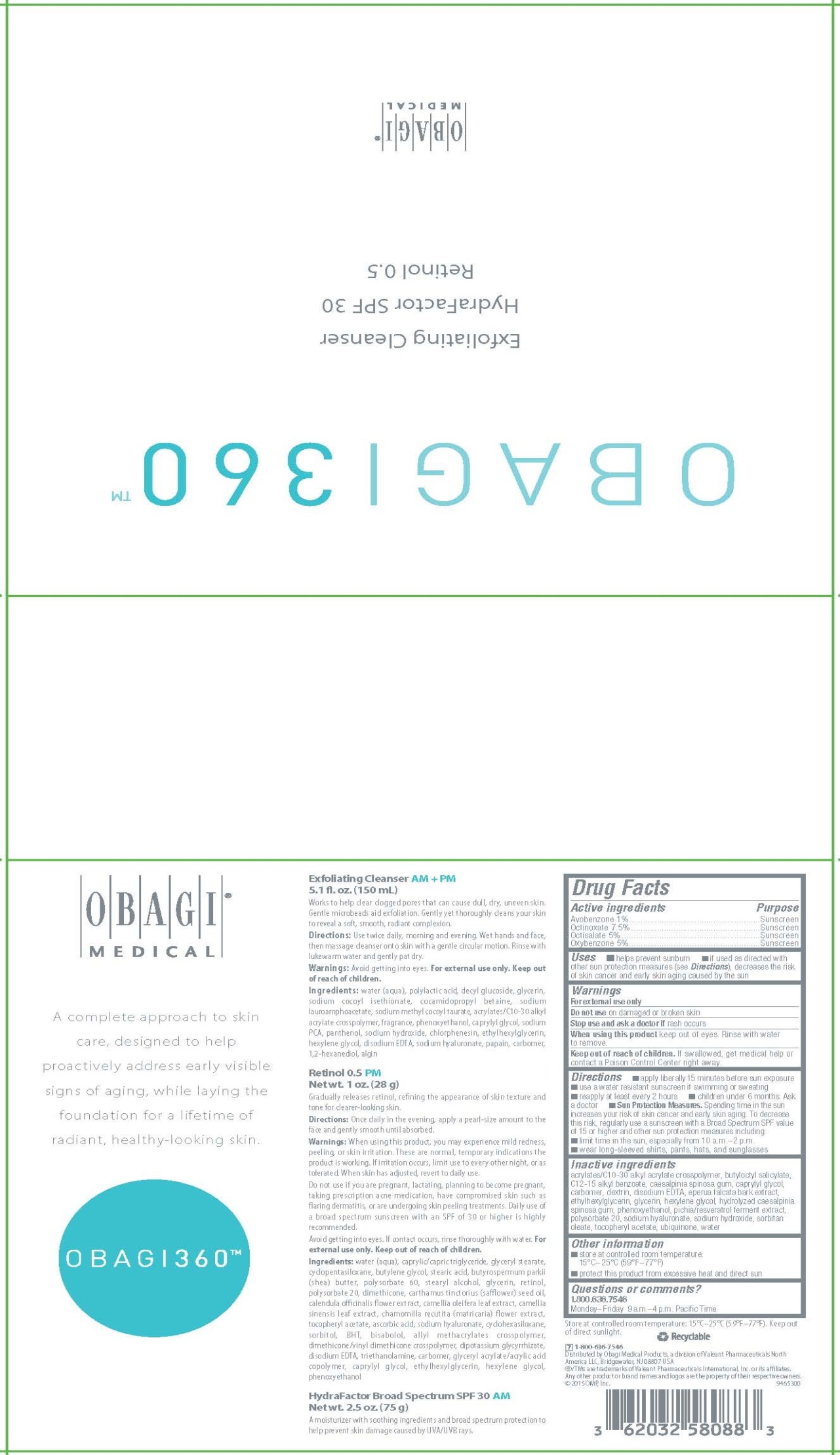 DRUG LABEL: Obagi 360
NDC: 62032-580 | Form: KIT | Route: TOPICAL
Manufacturer: OMP, Inc.
Category: otc | Type: HUMAN OTC DRUG LABEL
Date: 20190917

ACTIVE INGREDIENTS: AVOBENZONE 10 mg/1 g; OCTINOXATE 75 mg/1 g; OCTISALATE 50 mg/1 g; OXYBENZONE 50 mg/1 g
INACTIVE INGREDIENTS: CARBOMER COPOLYMER TYPE A (ALLYL PENTAERYTHRITOL CROSSLINKED); BUTYLOCTYL SALICYLATE; ALKYL (C12-15) BENZOATE; CAESALPINIA SPINOSA RESIN; CAPRYLYL GLYCOL; CARBOMER HOMOPOLYMER TYPE C (ALLYL PENTAERYTHRITOL CROSSLINKED); ICODEXTRIN; EDETATE DISODIUM; EPERUA FALCATA BARK; ETHYLHEXYLGLYCERIN; GLYCERIN; HEXYLENE GLYCOL; PHENOXYETHANOL; POLYSORBATE 20; HYALURONATE SODIUM; SODIUM HYDROXIDE; SORBITAN MONOOLEATE; .ALPHA.-TOCOPHEROL ACETATE; UBIDECARENONE; WATER

OBAGI 360™

Exfoliating Cleanser AM+PM

Works to help clear clogged pores that can cause dull, dry, uneven skin. Gentle microbeads aid exfoliation. Gently yet thoroughly cleans your skin to reveal a soft, smooth, radiant complexion.

Directions

Use twice daily, morning and evening. Wet hands and face, then massage cleanser onto skin with a gentle circular motion. Rinse with lukewarm water and gently pat dry.

Warnings

Avoid getting into eyes. For external use only. Keep out of reach of children.

Ingredients

water (aqua), polylactic acid, decyl glucoside, glycerin, sodium cocoyl isethionate, cocamidopropyl betaine, sodium lauroamphoacetate, sodium methyl cocoyl taurate, acrylates/C10-30 alkyl acrylate crosspolymer, fragrance, phenoxyethanol, caprylyl glycol, sodium PCA, panthenol, sodium hydroxide, chlorphenesin, ethylhexylglycerin, hexylene glycol, disodium EDTA, sodium hyaluronate, papain, carbomer, 1,2-hexanediol, algin

Retinol 0.5 PM

Gradually releases retinol, refining the appearance of skin texture and tone for clearer-looking skin.

Directions

Once daily in the evening, apply a pearl-size amount to the face and gently smooth until absorbed.

Warnings

When using this product, you may experience mild redness, peeling, or skin irritation. These are normal, temporary indications the product is working. If irritation occurs, limit use to every other night, or as tolerated. When skin has adjusted, revert to daily use.

Do not use if you are pregnant, lactating, planning to become pregnant, taking prescription acne medication, have compromised skin such as flaring dermatitis, or are undergoing skin peeling treatments. Daily use of a broad spectrum sunscreen with an SPF of 30 or higher is highly recommended.

Avoid getting into eyes. If contact occurs, rinse thoroughly with water. For external use only. Keep out of reach of children.

Ingredients

water (aqua), caprylic/capric triglyceride, glyceryl stearate, cyclopentasiloxane, butylene glycol, stearic acid, butyrospermum parkii (shea) butter, polysorbate 60, stearyl alcohol, glycerin, retinol, polysorbate 20, dimethicone, carthamus tinctorius (safflower) seed oil, calendula officinalis flower extract, camellia oleifera leaf extract, camellia sinensis leaf extract, chamomilla recutita (matricaria) flower extract, tocopheryl acetate, ascorbic acid, sodium hyaluronate, cyclohexasiloxane, sorbitol, BHT, bisabolol, allyl methacrylates crosspolymer, dimethicone/vinyl dimethicone crosspolymer, dipotassium glycyrrhizate, disodium EDTA, triethanolamine, carbomer, glyceryl acrylate/acrylic acid copolymer, caprylyl glycol, ethylhexylglycerin, hexylene, glycol, phenoxyethanol

HydraFactor Broad Spectrum SPF 30 AM

Drug Facts

Active ingredients

Avobenzone 1%
Octinoxate 7.5%

Octisalate 5%

Oxybenzone 5%

Purpose

Sunscreen

Uses

- helps prevent sunburn
- if used as directed with other sun protection measures (see Directions), decreases the risk of skin cancer and early skin aging caused by the sun

Warnings

For external use only

Do not use on damaged or broken skin

Stop use and ask a doctor if rash occurs

When using this product keep out of eyes. Rinse with water to remove.

Keep Out of Reach of Children

If swallowed, get medical help or contact a Poison Control Center right away.

Directions

- apply liberally 15 minutes before sun exposure
- use a water resistant sunscreen if swimming or sweating
- reapply at least every 2 hours
- children under 6 months: Ask a doctor
- Sun Protection Measures. Spending time in the sun increases your risk of skin cancer and early skin aging. To decrease this risk, regularly use a sunscreen with a Broad Spectrum SPF value of 15 or higher and other sun protection measures including:
  - limit time in the sun, especially from 10 a.m.–2 p.m.
  - wear long-sleeved shirts, pants, hats, and sunglasses

Inactive ingredients

acrylates/C10-30 alkyl acrylate crosspolymer, butyloctyl salicylate, C12-15 alkyl benzoate, caesalpinia spinosa gum, caprylyl glycol, carbomer, dextrin, disodium EDTA, eperua falcata bark extract, ethylhexylglycerin, glycerin, hexylene glycol, hydrolyzed caesalpinia spinosa gum, phenoxyethanol, pichia/resveratrol ferment extract, polysorbate 20, sodium hyaluronate, sodium hydroxide, sorbitan oleate, tocopheryl acetate, ubiquinone, water

Other information

- store at controlled room temperature: 15°C–25°C (59°F–77°F)
- protect this product from excessive heat and direct sun

Questions or comments?

1.800.636.7546
Monday–Friday 9 a.m.–4 p.m. Pacific Time

Principal Display Panel - Kit Carton

OBAGI 360™

Exfoliating Cleanser

HydraFactor SPF 30

Retinol 0.5

OBAGI®

MEDICAL